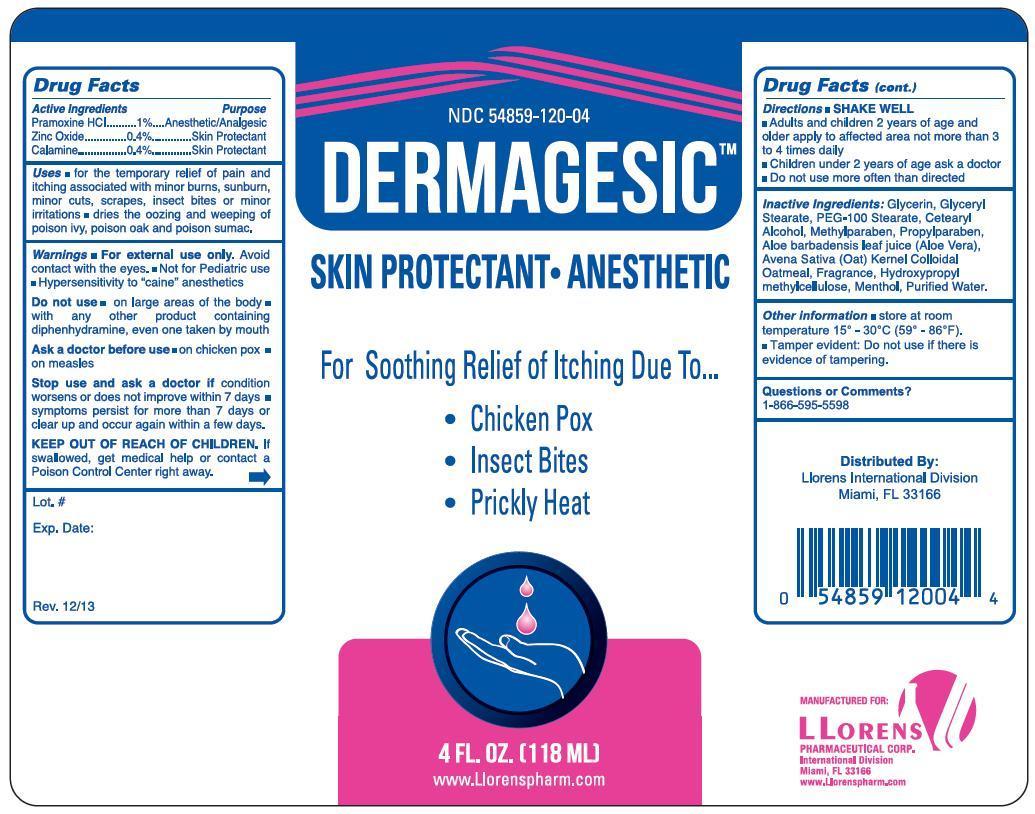 DRUG LABEL: Dermagesic
NDC: 54859-120 | Form: LIQUID
Manufacturer: Llorens Pharmaceuticals International Division
Category: otc | Type: HUMAN OTC DRUG LABEL
Date: 20251231

ACTIVE INGREDIENTS: PRAMOXINE HYDROCHLORIDE 1 mg/100 mL; ZINC OXIDE 0.4 mg/100 mL; FERRIC OXIDE RED 0.4 mg/100 mL
INACTIVE INGREDIENTS: GLYCERIN; GLYCERYL STEARATE SE; PEG-100 STEARATE; CETOSTEARYL ALCOHOL; METHYLPARABEN; PROPYLPARABEN; ALOE VERA LEAF; AVENA SATIVA WHOLE; HYPROMELLOSE 2208 (100 MPA.S); MENTHOL; WATER

Llorens-Dermagesic Liquid 120

Active Ingredients Purpose

Pramozine HCl .... 1% ............ Anesthetic/Analgesic

Zinc Oxide .........0.4% ............ Skin Protectant

Calamine ...........0.4% ............ Skin Protectant

Purpose

Anesthetic/Analgesic

Skin Protectant

Uses

- for the temporary relief of pain and itching associated with minor burns, sunburn, minor cuts, scrapes, insect bites or minor irritations
- dries the oozing and weeping of poison ivy, poison oak and poison sumac.

Warnings

- For external use only. Avoid contact with the eyes
- Not for Pediatric use
- Hypersensitivity to "caine" anesthetics

Do not use

- on large areas of the body
- with any other product containing diphenhydramine, even one taken by mouth

Ask a doctor before use

- on chicken pox
- on measles

Stop use and ask a doctor ifcondition worsens or does not improve within 7 days

- symptoms persist for more than 7 days or clear up and occur again within a few days

KEEP OUT OF REACH OF CHILDREN

KEEP OUT OF REACH OF CHILDRENIf swallowed, get medical help or contact a Poison Control Center right away.

DOSAGE AND ADMINISTRATION

Directions SHAKE WELL

- Adults and children 2 years of age and older apply to affected area not more than 3 to 4 times daily
- Children under 2 years of age ask a doctor
- Do not use more often than directed

INACTIVE INGREDIENT

Inactive Ingredients: Glycerin, glyceryl stearate, PEG-100 Stearate, cetearyl alcohol, methylparaben, propylparaben, aloe barbadensis leaf juic (aloe vera), avena sativa (oat) kernel colloidal oatmeal, fregrance, hydroxypropyl methylcellulose, menthol, purified water

Questions: 1-866-595-5598